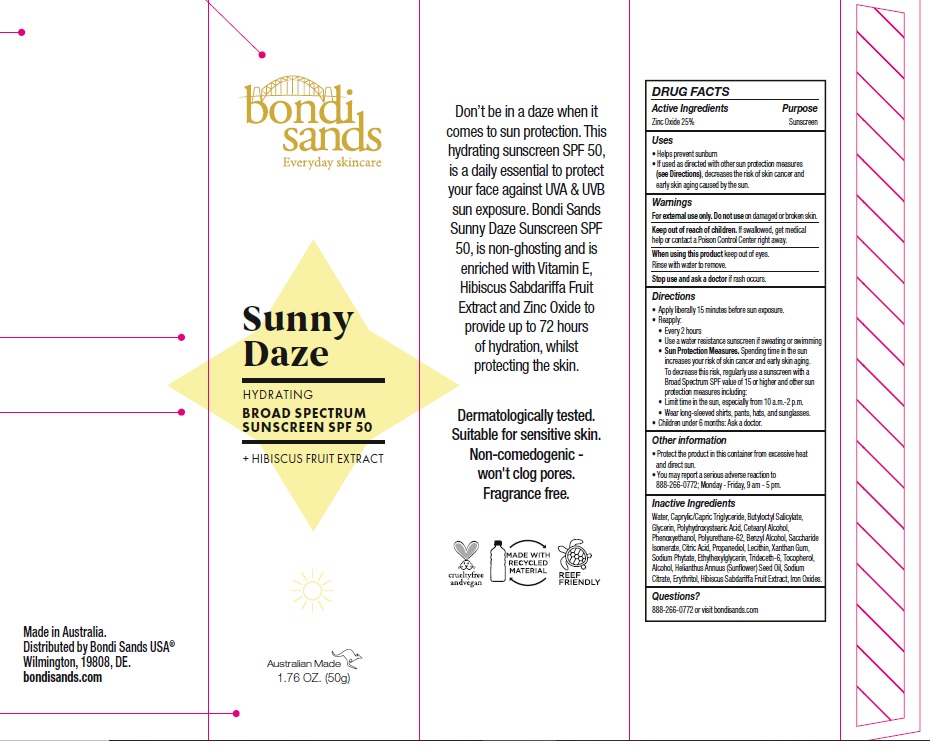 DRUG LABEL: BONDI SANDS SUNNY DAZE HYDRATING BROAD SPECTRUM SUNSCREEN SPF 50
NDC: 79950-014 | Form: LOTION
Manufacturer: BONDI SANDS (USA) INC.
Category: otc | Type: HUMAN OTC DRUG LABEL
Date: 20241106

ACTIVE INGREDIENTS: ZINC OXIDE 250 mg/1 g
INACTIVE INGREDIENTS: POLYURETHANE-62; CITRIC ACID MONOHYDRATE; TRIDECETH-6; FERRIC OXIDE YELLOW; FERROSOFERRIC OXIDE; ALCOHOL; ERYTHRITOL; SODIUM CITRATE; XANTHAN GUM; HIBISCUS SABDARIFFA WHOLE; FERRIC OXIDE RED; SUNFLOWER OIL; PROPANEDIOL; PHENOXYETHANOL; BUTYLOCTYL SALICYLATE; POLYHYDROXYSTEARIC ACID (2300 MW); CETOSTEARYL ALCOHOL; WATER; PHYTATE SODIUM; MEDIUM-CHAIN TRIGLYCERIDES; TOCOPHEROL; BENZYL ALCOHOL; SACCHARIDE ISOMERATE; GLYCERIN; ETHYLHEXYLGLYCERIN; LECITHIN, SOYBEAN

BONDI SANDS SUNNY DAZE HYDRATING BROAD SPECTRUM SUNSCREEN SPF 50

Active Ingredients

Zinc Oxide 25%

Purpose

Sunscreen

Uses

- Helps prevent sunburn
- If used as directed with other sun protection measures (see Directions), decreases the risk of skin cancer and early skin aging caused by the sun.

Warnings

For external use only

Do not use

on damaged or broken skin.

Keep out of reach of children.

If swallowed, get medical help or contact a Poison Control Center right away.

When using this product

keep out of eyes. Rinse with water to remove.

Stop use and ask a doctor

if rash occurs.

Directions

- Apply liberally 15 minutes before sun exposure.
- Reapply:
- Every 2 hours
- Use a water resistant sunscreen if swimming or sweating.
- Sun Protection Measures. Spending time in the sun increases your risk of skin cancer and early skin aging. To decrease this risk, regularly use a sunscreen with a Broad Spectrum SPF value of 15 or higher and other sun protection measures including:
- Limit time in the sun, especially from 10 a.m.- 2 p.m.
- Wear long-sleeved shirts, pants, hats, and sunglasses.
- Children under 6 months: Ask a doctor.

Other information

- Protect the product in this container from excessive heat and direct sun.
- You may report a serious adverse reaction to 888-266-0772; Monday – Friday, 9 am – 5 pm.

Inactive Ingredients

Water, Caprylic/Capric Triglyceride, Butyloctyl Salicylate, Glycerin, Polyhydroxystearic Acid, Cetearyl Alcohol, Phenoxyethanol, Polyurethane-62, Benzyl Alcohol, Saccharide Isomerate, Citric Acid, Propanediol, Lecithin, Xanthan Gum, Sodium Phytate, Ethylhexylglycerin, Trideceth-6, Tocopherol, Alcohol, Helianthus Annuus (Sunflower) Seed Oil, Sodium Citrate, Erythritol, Hibiscus Sabdariffa Fruit Extract, Iron Oxides.

Questions?

888-266-0772 or visit bondisands.com

Company Information

Made in Australia.

Distributed by Bondi Sands USA

Wilmington, DE 19808

Product Packaging

bondi sands

Everyday skincare

Sunny

Daze

HYDRATING

BROAD SPECTRUM

SUNSCREEN SPF 50

+ HIBISCUS FRUIT EXTRACT

Australian Made

1.76 OZ. (50g)